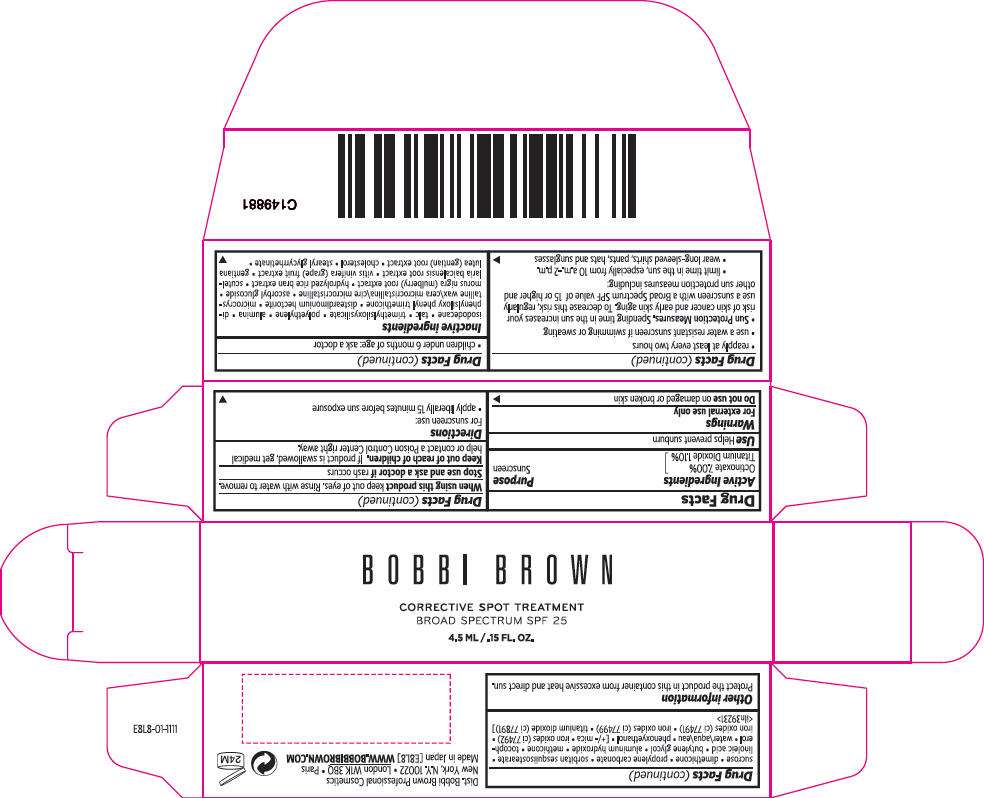 DRUG LABEL: BOBBIE BROWN CORRECTIVE SPOT TREATMENT BROAD SPECTRUM 
NDC: 64141-113 | Form: CREAM
Manufacturer: Bobbi Brown Professional Cosmetics Inc.
Category: otc | Type: HUMAN OTC DRUG LABEL
Date: 20121004

ACTIVE INGREDIENTS: OCTINOXATE 98 mg/1 mL; TITANIUM DIOXIDE 15.4 mg/1 mL
INACTIVE INGREDIENTS: isododecane; talc; high density polyethylene; aluminum oxide; diphenylsiloxy phenyl trimethicone; microcrystalline wax; ascorbyl glucoside; morus nigra root; scutellaria baicalensis root; wine grape; gentiana lutea root; cholesterol; stearyl glycyrrhetinate; sucrose; dimethicone; propylene carbonate; linoleic acid; butylene glycol; aluminum hydroxide; tocopherol; water; phenoxyethanol; mica; ferric oxide yellow; ferric oxide red; ferrosoferric oxide

CORRECTIVE SPOT TREATMENT BROAD SPECTRUM SPF 25

Active Ingredients

Octinoxate 7.00%
Titanium Dioxide 1.10%

Purpose

Sunscreen

Use

Helps prevent sunburn

Warnings

For external use only

Do not use on damaged or broken skin

When using this product keep out of eyes. Rinse with water to remove.

Stop use and ask a doctor if rash occurs

Keep out of reach of children. If product is swallowed, get medical help or contact a Poison Control Center right away.

Directions

For sunscreen use:

- apply liberally 15 minutes before sun exposure
- reapply at least every two hours
- use a water resistant sunscreen if swimming or sweating
- Sun Protection Measures. Spending time in the sun increases your risk of skin cancer and early skin aging. To decrease this risk, regularly use a sunscreen with a Broad Spectrum SPF value of 15 or higher and other sun protection measures including:
  - limit time in the sun, especially from 10 a.m.-2 p.m.
  - wear long-sleeved shirts, pants, hats and sunglasses
- children under 6 months of age: ask a doctor

Inactive ingredients

isododecane • talc • trimethylsiloxysilicate • polyethylene • alumina • diphenylsiloxy phenyl trimethicone • disteardimonium hectorite • microcrystalline wax\cera microcristallina\cire microcristalline • ascorbyl glucoside • morus nigra (mulberry) root extract • hydrolyzed rice bran extract • scutellaria baicalensis root extract • vitis vinifera (grape) fruit extract • gentiana lutea (gentian) root extract • cholesterol • stearyl glycyrrhetinate • sucrose • dimethicone • propylene carbonate • sorbitan sesquiisostearate • linoleic acid • butylene glycol • aluminum hydroxide • methicone • tocopherol • water\aqua\eau • phenoxyethanol • [+/- mica • iron oxides (ci 77492) • iron oxides (ci 77491) • iron oxides (ci 77499) • titanium dioxide (ci 77891)] <iln39231>

Other information

Protect the product in this container from excessive heat and direct sun.

Dist. Bobbi Brown Professional Cosmetics
New York, N.Y. 10022

PRINCIPAL DISPLAY PANEL - 4.5 ML Tube Carton

BOBBI BROWN

CORRECTIVE SPOT TREATMENT
BROAD SPECTRUM SPF 25

4.5 ML / .15 FL. OZ.